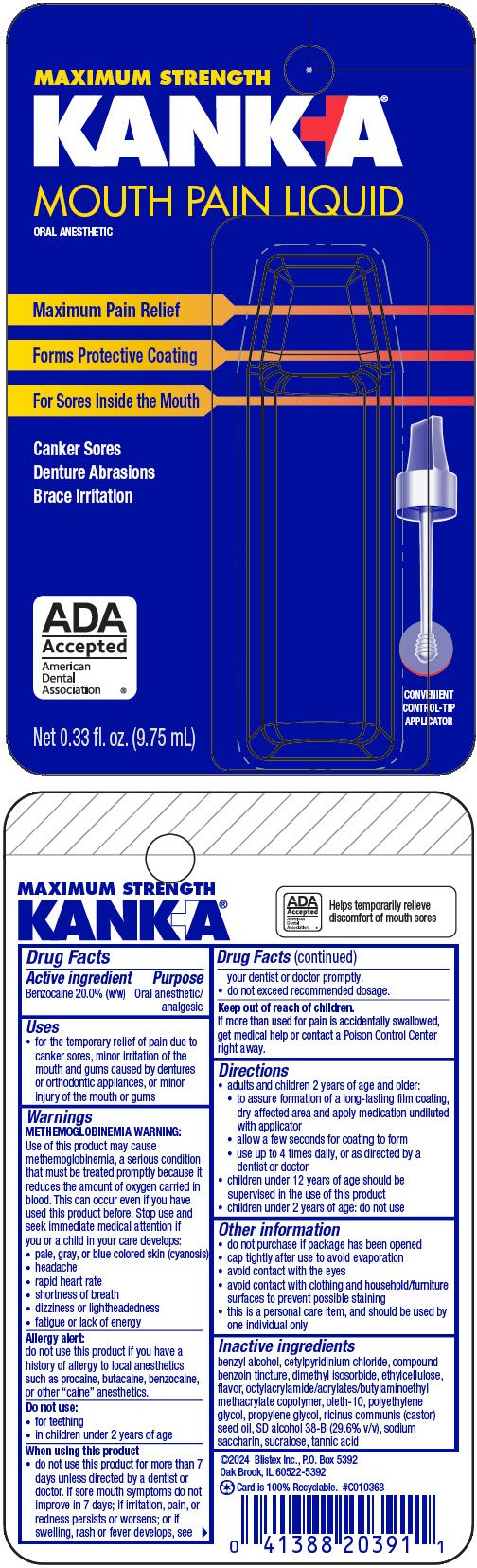 DRUG LABEL: Kank-A 
NDC: 10157-9477 | Form: LIQUID
Manufacturer: Blistex Inc.
Category: otc | Type: HUMAN OTC DRUG LABEL
Date: 20241217

ACTIVE INGREDIENTS: Benzocaine 200 mg/1 mL
INACTIVE INGREDIENTS: BENZYL ALCOHOL; CETYLPYRIDINIUM CHLORIDE; compound benzoin tincture; DIMETHYL ISOSORBIDE; ETHYLCELLULOSE, UNSPECIFIED; ACRYLATE/BUTYLAMINOETHYL METHACRYLATE/METHYL ACRYLATE/METHYL METHACRYLATE/OCTYLACRYLAMIDE COPOLYMER (40000 WAMW); OLETH-10; POLYETHYLENE GLYCOL, UNSPECIFIED; POLYETHYLENE GLYCOL 300; PROPYLENE GLYCOL; CASTOR OIL; ALCOHOL; SACCHARIN SODIUM; SUCRALOSE; TANNIC ACID

Kank-A®
Mouth Pain Liquid

Drug Facts

Active ingredient

Benzocaine 20.0% (w/w)

Purpose

Oral anesthetic/analgesic

Uses

- for the temporary relief of pain due to canker sores, minor irritation of the mouth and gums caused by dentures or orthodontic appliances, or minor injury of the mouth or gums

Warnings

METHEMOGLOBINEMIA WARNING

Use of this product may cause methemoglobinemia, a serious condition that must be treated promptly because it reduces the amount of oxygen carried in blood. This can occur even if you have used this product before. Stop use and seek immediate medical attention if you or a child in your care develops:

- pale, gray, or blue colored skin (cyanosis)
- headache
- rapid heart rate
- shortness of breath
- dizziness or lightheadedness
- fatigue or lack of energy

Allergy alert

do not use this product if you have a history of allergy to local anesthetics such as procaine, butacaine, benzocaine, or other "caine" anesthetics.

Do not use

- for teething
- in children under 2 years of age

When using this product

- do not use this product for more than 7 days unless directed by a dentist or doctor. If sore mouth symptoms do not improve in 7 days; if irritation, pain, or redness persists or worsens; or if swelling, rash or fever develops, see your dentist or doctor promptly.
- do not exceed recommended dosage.

Keep out of reach of children. If more than used for pain is accidentally swallowed, get medical help or contact a Poison Control Center right away.

Directions

- adults and children 2 years of age and older:
  - to assure formation of a long-lasting film coating, dry affected area and apply medication undiluted with applicator
  - allow a few seconds for coating to form
  - use up to 4 times daily, or as directed by a dentist or doctor
  - children under 12 years of age should be supervised in the use of this product
  - children under 2 years of age: do not use

Other information

- do not purchase if package has been opened
- cap tightly after use to avoid evaporation
- avoid contact with the eyes
- avoid contact with clothing and household/furniture surfaces to prevent possible staining
- this is a personal care item, and should be used by one individual only

Inactive ingredients

benzyl alcohol, cetylpyridinium chloride, compound benzoin tincture, dimethyl isosorbide, ethylcellulose, flavor, octylacrylamide/acrylates/butylaminoethyl methacrylate copolymer, oleth-10, polyethylene glycol, propylene glycol, ricinus communis (castor) seed oil, SD alcohol 38-B (29.6% v/v), sodium saccharin, sucralose, tannic acid

PRINCIPAL DISPLAY PANEL - 9.75 mL Bottle Package

MAXIMUM STRENGTH
KANK-A®
MOUTH PAIN LIQUID
ORAL ANESTHETIC

Maximum Pain Relief

Forms Protective Coating

For Sores Inside the Mouth

Canker Sores
Denture Abrasions
Brace Irritation

ADA
Accepted
American
Dental
Association ®

CONVENIENT
CONTROL-TIP
APPLICATOR

Net 0.33 fl. oz. (9.75 mL)